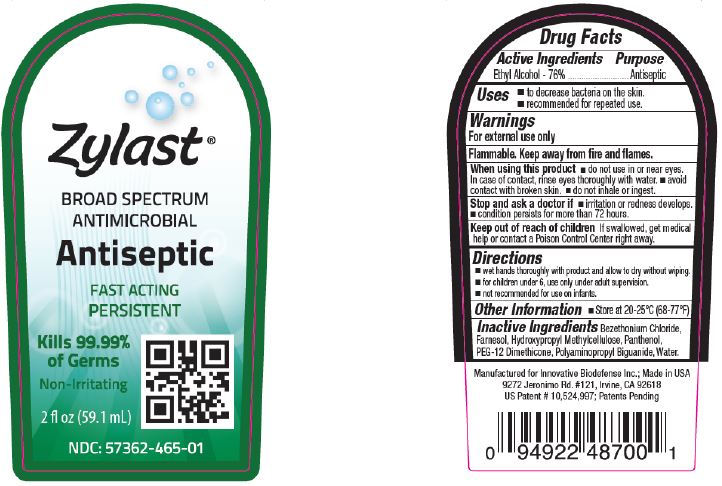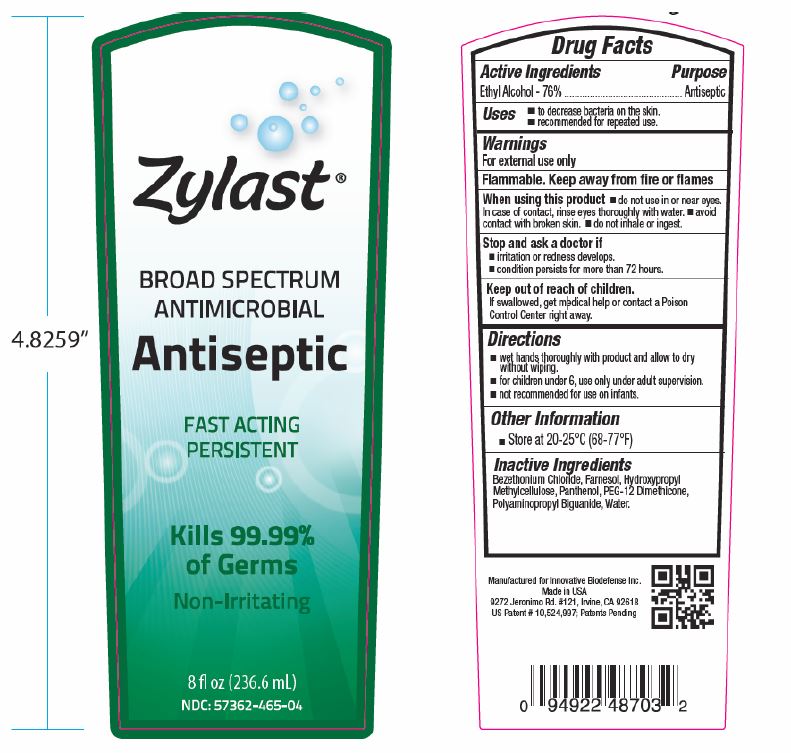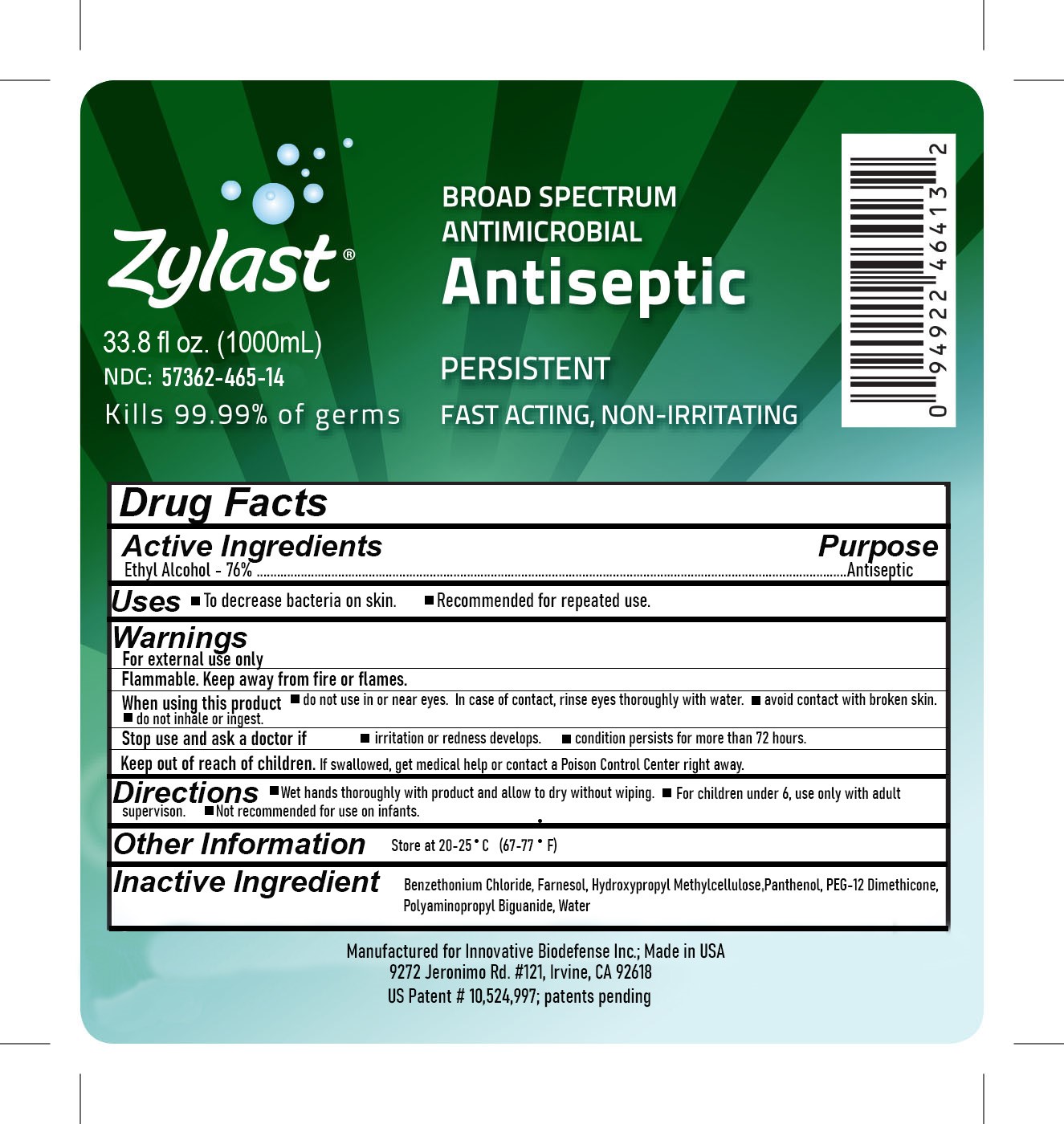 DRUG LABEL: Zylast Antiseptic
NDC: 57362-465 | Form: GEL
Manufacturer: Innovative BioDefense
Category: otc | Type: HUMAN OTC DRUG LABEL
Date: 20251002

ACTIVE INGREDIENTS: ALCOHOL 44.9 mL/59.1 mL
INACTIVE INGREDIENTS: WATER

Zylast Antiseptic

ACTIVE INGREDIENT

Ethyl Alcohol - 76%

PURPOSE

Antiseptic

INDICATIONS AND USAGE

- To decrease bacteria on skin.
- Recommended for repeated use.

WARNINGS

- For external use only
- Flammable. Keep away fro fire and flames,
- When using this product, do not use in or near eyes. In case of contact, rinse eyes thoroughly with water. Avoid contact with broken skin. Do not inhale or ingest.

ASK DOCTOR

Stop and ask a doctor if irritation or redness develops, condition persists for more than 72 hours.

KEEP OUT OF REACH OF CHILDREN

If swallowed, get medical help or contact a Poison Control Center right away.

DOSAGE AND ADMINISTRATION

- Wet hands thoroughly with product and allow to dry without wiping.
- for children under 6, use only under adult supervision.
- not recommended for use on infants.

INACTIVE INGREDIENT

Benzethonium Chloride, Farnesol, Hydroxypropyl Methylcellulose, Panthenol, PEG-12 Dimethicone, Polyaminopropyl Biguanide, Water

- Warnings
- Uses
- Stop and ask a doctor
- Directions
- Keep out of reach of children
- Inactive Ingredient

PACKAGE LABEL

NDC 57362-465-01

Zylast Antiseptic

Antiseptic

2oz

NDC 57362-465-04

Zylast Antiseptic

Antiseptic

8 oz

NDC 57362-465-14

Zylast Antiseptic

Antiseptic

1000 mL